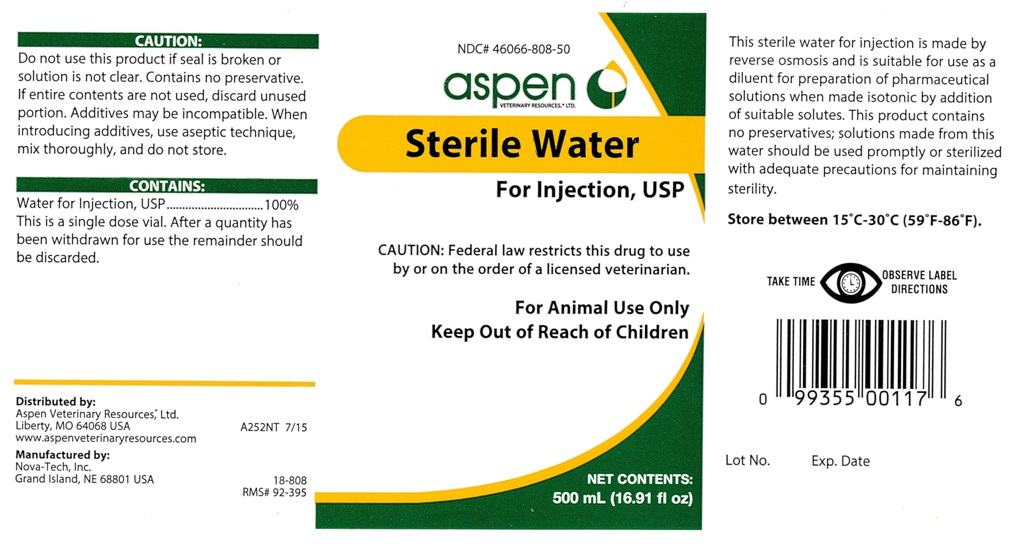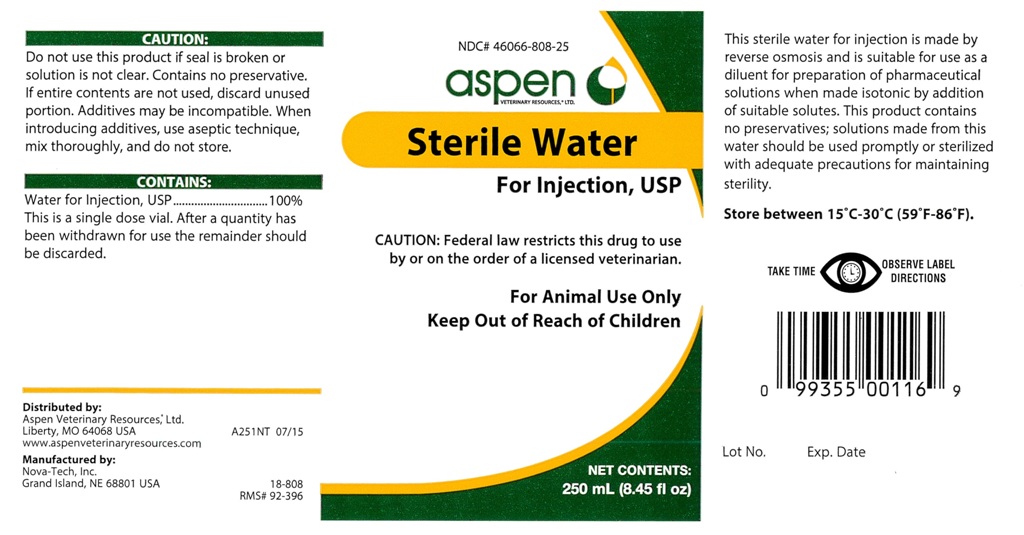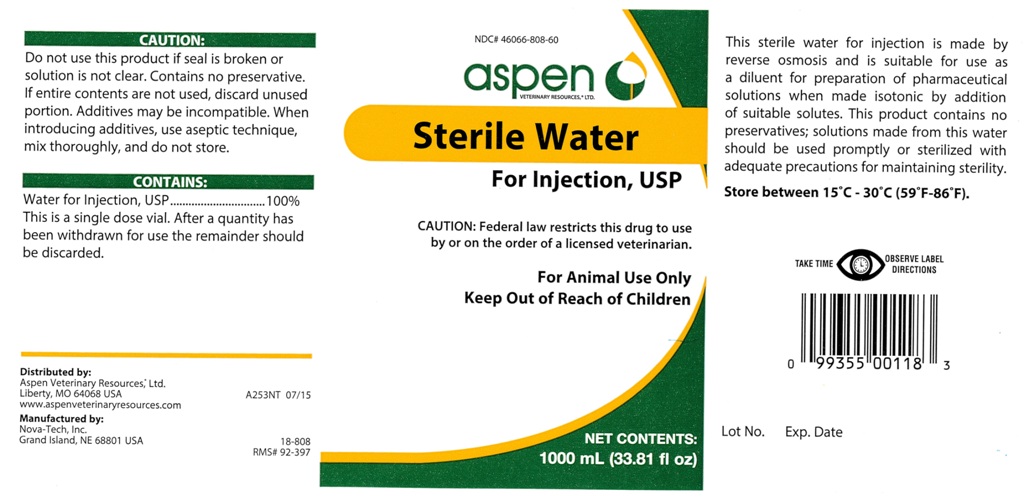 DRUG LABEL: Sterile Water
NDC: 46066-808 | Form: INJECTION
Manufacturer: Aspen Veterinary
Category: animal | Type: PRESCRIPTION ANIMAL DRUG LABEL
Date: 20160803

ACTIVE INGREDIENTS: WATER 250 mL/250 mL

Sterile Water for Injection, USP

CAUTION:

Do not use this product if seal is broken or
solution is not clear. Contains no preservative.
If entire contents are not used, discard unused
portion. Additives may be incompatible. When
introducing additives, use aseptic technique,
mix thoroughly, and do not store.

CONTAINS:

Water for Injection, USP...... 100%
This is a single dose vial. After a quantity has
been withdrawn for use the remainder should
be discarded.

PRECAUTIONS

CAUTION: Federal law restricts this drug to use
by or on the order of a licensed veterinarian.

VETERINARY INDICATIONS

For Animal Use Only

Keep Out of Reach of Children

INFORMATION FOR OWNERS/CAREGIVERS

NET CONTENTS:
1000 mL (33.81 fl oz)

INFORMATION FOR OWNERS/CAREGIVERS

This sterile water for injection is made by
reverse osmosis and is suitable for use as
a diluent for preparation of pharmaceutical
solutions when made isotonic by addition
of suitable solutes. This product contains no
preservatives; solutions made from this water
should be used promptly or sterilized with
adequate precautions for maintaining sterility.

STORAGE AND HANDLING

Store between 15 degrees C - 30 degrees C (59 degrees F - 86 degrees F).

INFORMATION FOR OWNERS/CAREGIVERS

Distributed by:Aspen Veterinary Resources®, Ltd.Liberty, MO 64068 USA A253NT 07/15
www.aspenaveterinaryresources.com

Manufactured by:Nova-Tech, Inc.Grand Island, NE 68801 USA

18-808
RMS# 92-397

Lot No. Exp. Date

WARNINGS AND PRECAUTIONS

TAKE TIME OBSERVE LABEL DIRECTIONS